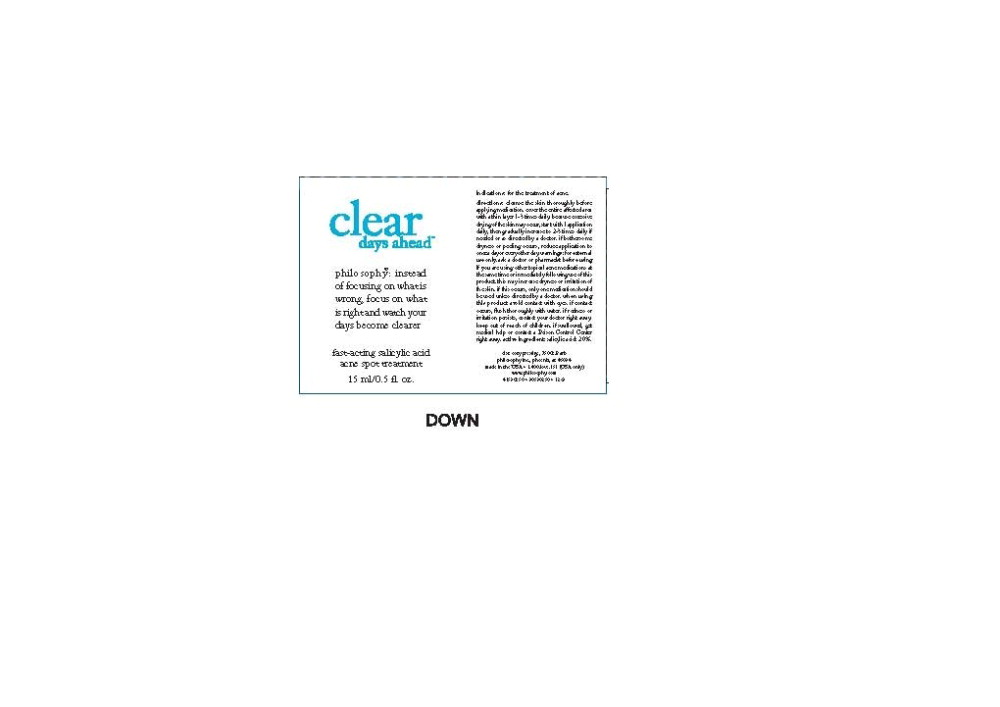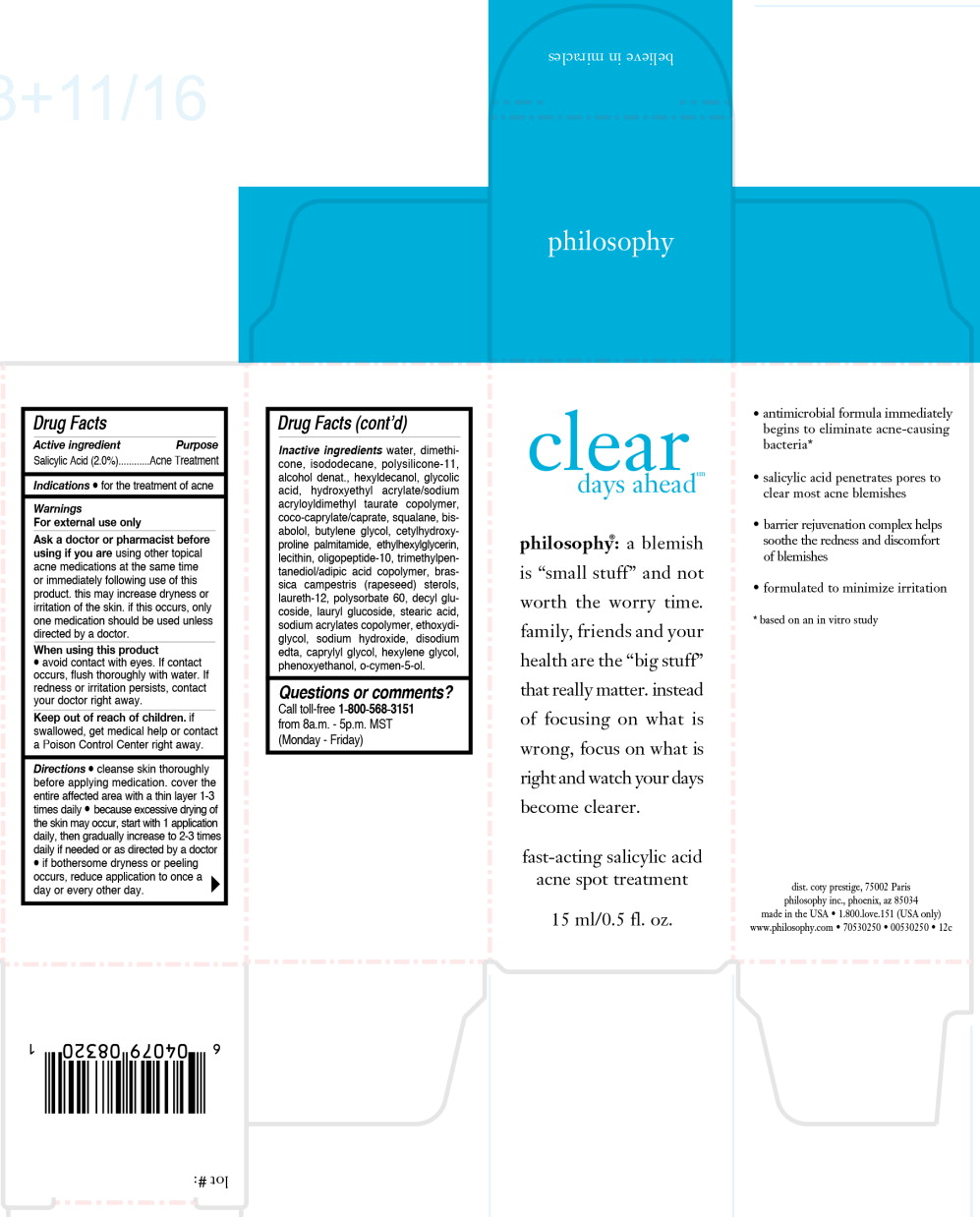 DRUG LABEL: clear days ahead
NDC: 50184-1020 | Form: GEL
Manufacturer: Philosophy
Category: otc | Type: HUMAN OTC DRUG LABEL
Date: 20251217

ACTIVE INGREDIENTS: SALICYLIC ACID 0.3 g/15 mL
INACTIVE INGREDIENTS: WATER; DIMETHICONE; ISODODECANE; HEXYLDECANOL; GLYCOLIC ACID; SQUALANE; LEVOMENOL; BUTYLENE GLYCOL; PALMITAMIDE; ETHYLHEXYLGLYCERIN; RAPESEED STEROL; LAURETH-12; POLYSORBATE 60; DECYL GLUCOSIDE; LAURYL GLUCOSIDE; STEARIC ACID; SODIUM HYDROXIDE; EDETATE DISODIUM; CAPRYLYL GLYCOL; HEXYLENE GLYCOL; PHENOXYETHANOL; O-CYMEN-5-OL

Drug Facts

Active ingredient

Salicylic Acid (2.0%)

Purpose

Acne Treatment

Indications

- for the treatment of acne

Warnings

For external use only

Ask a doctor or pharmacist before using if you are using other topical acne medications at he same time or immediately following use of this product. this may increase dryness or irritation of the skin. if this occurs, only one medication should be used unless directed by a doctor.

When using this product

- avoid contact with eyes. If contact occurs, flush thoroughly with water. If redness or irritation persists, contact your doctor right away.

Keep out of reach of children.

- If swallowed, get medical help or contact a Poison Control Center right away.

Directions

- cleanse skin thoroughly before applying medication. cover the entire affected area with a thin layer 1-3 times daily
- because excessive drying of the skin may occur, start with 1 application daily, then gradually increase to 2-3 times daily if needed or as directed by a doctor
- if bothersome dryness or peeling occurs, reduce application to once a day or every other day.

Inactive ingredients

water, dimethicone, isododecane, polysilicone-11, alcohol denat., hexyldecanol, glycolic acid, hydroxyethyl acrylate/sodium acryloyldimethyl taurate copolymer, coco-caprylate/caprate, squalane, bisabolol, butylene glycol, cetylhydroxyproline palmitamide, ethylhexylglycerin, lecithin, oligopeptide-10, trimethylpentanediol/ adipic acid copolymer, rassica campestris (rapeseed) sterols, laureth-12, polysorbate 60, decyl glucoside, lauryl glucoside, stearic acid, sodium acrylates copolymer, ethoxydiglycol, sodium hydroxide, disodium edta, aprylyl glycol, hexylene glycol, phenoxyethanol, o-cymen-5-ol.

Questions or comments?

Call toll-free 1-800-568-3151 from 8a.m. - 5p.m. MST

(Monday - Friday)

Principal Display Panel - 15 ml Bottle Label

clear

days ahead™

philosophy®: instead
of focusing on what is
wrong, focus on what
is right and watch your
days become clearer

fast-acting salicylic acid

acne spot treatment

15 ml/0.5 fl oz.

Principal Display Panel - 15 ml Box Label

clear

days ahead™

philosophy®: a blemish
is “small stuff” and not
worth the worry time.
family, friends and your
health are the “big stuff”
that really matter. Instead
of focusing on what is
wrong, focus on what is
right and watch your days
become clearer.

fast-acting salicylic acid

acne spot treatment

15 ml/0.5 fl. oz.